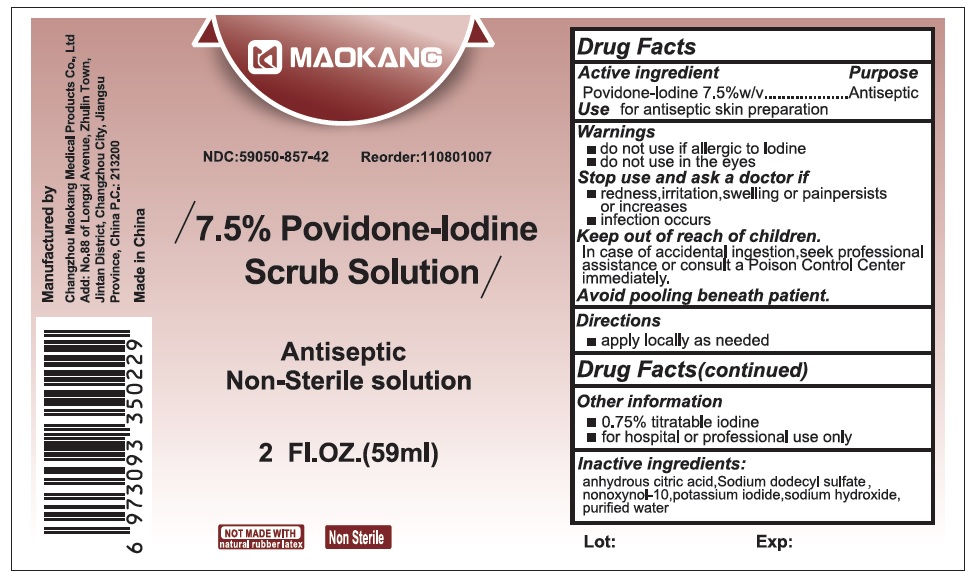 DRUG LABEL: Maokang Povidone-Iodine Antiseptic
NDC: 59050-857 | Form: LIQUID
Manufacturer: Changzhou Maokang Medical Products Co
Category: otc | Type: HUMAN OTC DRUG LABEL
Date: 20260223

ACTIVE INGREDIENTS: POVIDONE-IODINE 75 mg/1 mL
INACTIVE INGREDIENTS: ANHYDROUS CITRIC ACID; SODIUM LAURYL SULFATE; NONOXYNOL-10; POTASSIUM IODIDE; SODIUM HYDROXIDE; WATER

Maokang 7.5% Povidone-Iodine Antiseptic

Active ingredient

Povidone-lodine 7.5%w/v

Purpose

Antiseptic

Use

for antiseptic skin preparation

Warnings

• do not use if allergic to Iodine
• do not use in the eyes

Stop use and ask a doctor if

• redness,irritation,swelling or painpersists or increases
• infection occurs

Keep out of reach of children.

In case of accidental ingestion,seek professional assistance or consult a poison Control Center immediately.

Avoid pooling beneath patient.

Directions

• apply locally as needed

Other information

- 0.75% titratable iodine
- for hospital or professional use only

Inactive ingredients:

anhydrous citric acid, Sodium dodecyl sulfate, nonoxynol-10, potassium iodide, sodium hydroxide, purified water